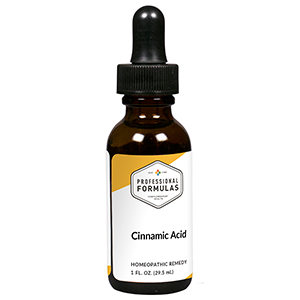 DRUG LABEL: Cinnamic Acid
NDC: 63083-1511 | Form: LIQUID
Manufacturer: Professional Complementary Health Formulas
Category: homeopathic | Type: HUMAN OTC DRUG LABEL
Date: 20190815

ACTIVE INGREDIENTS: CINNAMIC ACID 9 [hp_X]/29.5 mL
INACTIVE INGREDIENTS: ALCOHOL; WATER

YCIN

ACTIVE INGREDIENTS

Cinnamic acid 9X, 12X, 30X, 60X

QUESTIONS

Professional Formulas

PO Box 2034 Lake Oswego, OR 97035

INDICATIONS

For the temporary relief of irritated skin, itching, general fatigue, occasional headache, or indigestion due to sensitivity to phenolic compounds found in foods or other products.*

PURPOSE

*Claims based on traditional homeopathic practice, not accepted medical evidence. Not FDA evaluated.

WARNINGS

In case of overdose, get medical help or contact a poison control center right away.

Keep out of the reach of children.

PREGNANCY OR BREAST FEEDING

If pregnant or breastfeeding, ask a healthcare professional before use.

DIRECTIONS

Place drops under tongue 30 minutes before/after meals. Adults and children 12 years and over: Take 10 drops up to 3 times per day. Consult a physician for use in children under 12 years of age.

OTHER INFORMATION

Tamper resistant. If seal is broken, do not use. After opening, close container tightly and store at room temperature away from heat.

INACTIVE INGREDIENTS

20% ethanol, purified water.

LABEL

Est 1985

Professional Formulas

Complementary Health

Cinnamic Acid

Homeopathic Remedy

1 FL. OZ. (29.5 mL)